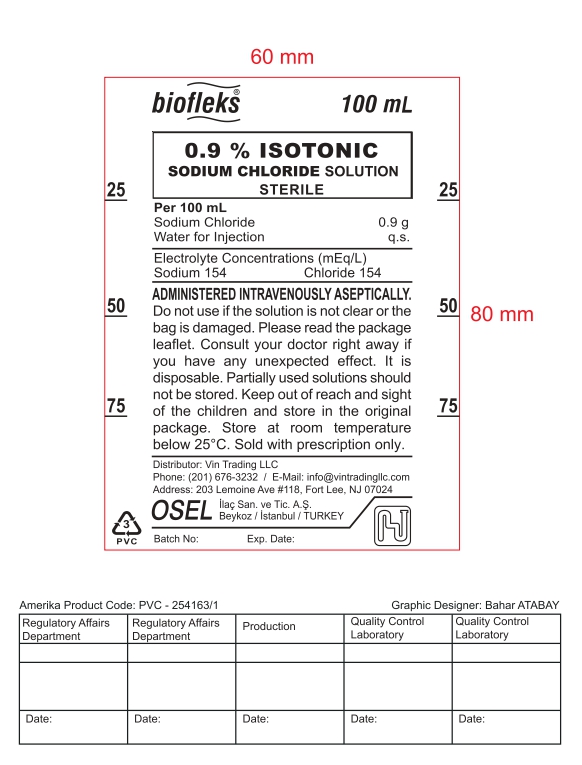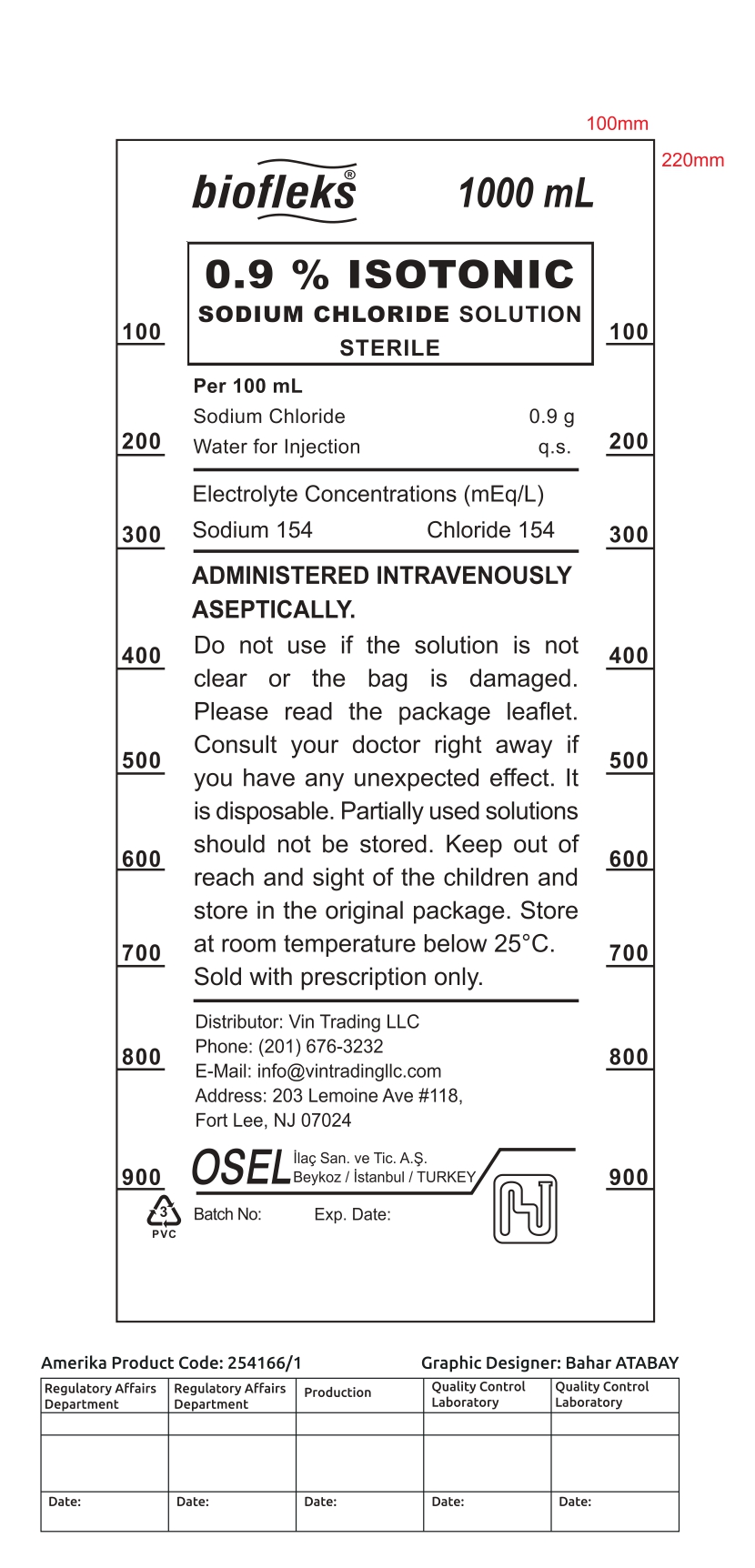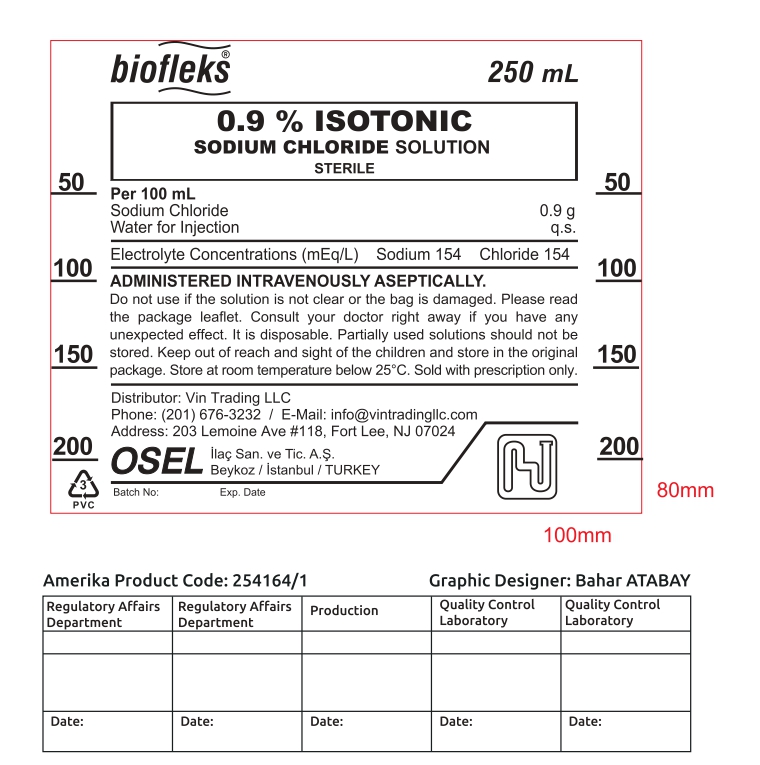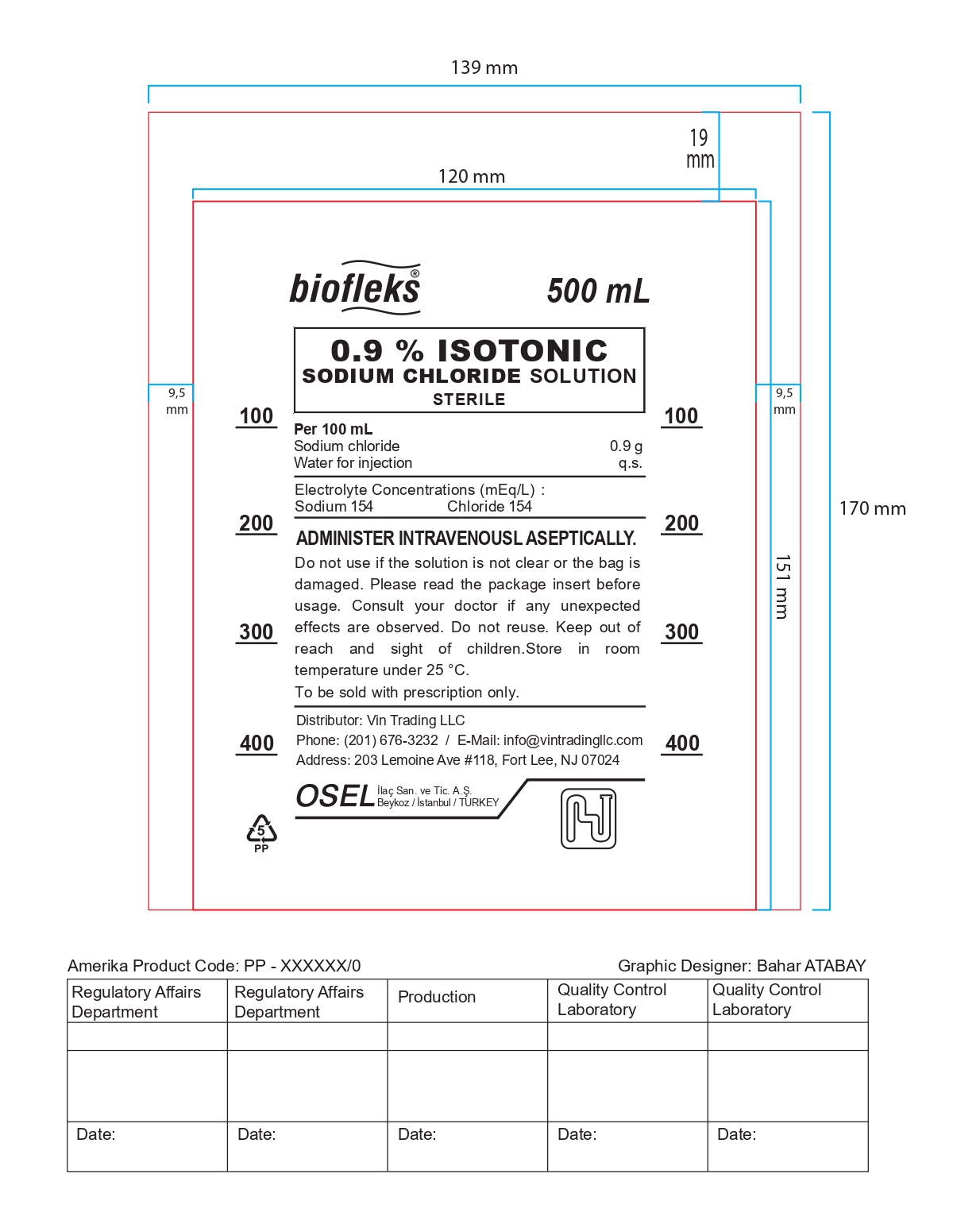 DRUG LABEL: ISOTONIC SODIUM CHLORIDE
NDC: 85184-0001 | Form: INJECTION
Manufacturer: HAVER FARMA ILAC ANONIM SIRKETI
Category: prescription | Type: HUMAN PRESCRIPTION DRUG LABEL
Date: 20250505

ACTIVE INGREDIENTS: SODIUM CHLORIDE 0.9 g/100 mL
INACTIVE INGREDIENTS: WATER

GENERAL PRECAUTIONS

ADMINISTERED INTRAVENOUSLY ASEPTICALLY. Do not use if the solution is not clear or the bag is damaged. Please read the package leaflet. Consult your doctor right away if you have any unexpected effect. It is disposable. Partially used solutions should not be stored. Keep out of reach and sight of the children and store in the original package. Store at room temperature below 25°C. Sold with prescription only.

PACKAGE LABEL

biofleks
100 mL
0.9 % ISOTONIC
SODIUM CHLORIDE SOLUTION
STERILE

Per 100 mL
Sodium Chloride
Water for Injection

Electrolyte Concentrations (mEq/L)
ADMINISTERED INTRAVENOUSLY ASEPTICALLY. Do not use if the solution is not clear or the bag is damaged. Please read the package leaflet. Consult your doctor right away if you have any unexpected effect. It is disposable. Partially used solutions should not be stored. Keep out of reach and sight of the children and store in the original package. Store at room temperature below 25°C. Sold with prescription only. Distributor: Vin Trading LLC
Phone: (201) 676-3232 / E-Mail: info@vintradingllc.com Address: 203 Lemoine Ave #118, Fort Lee, NJ 07024
OSEL llaç San. ve Tic. A.Ş.
Beykoz / İstanbul / TURKEY

100mL Bag

250mL Bag

500 mL Bag

1000mL Bag